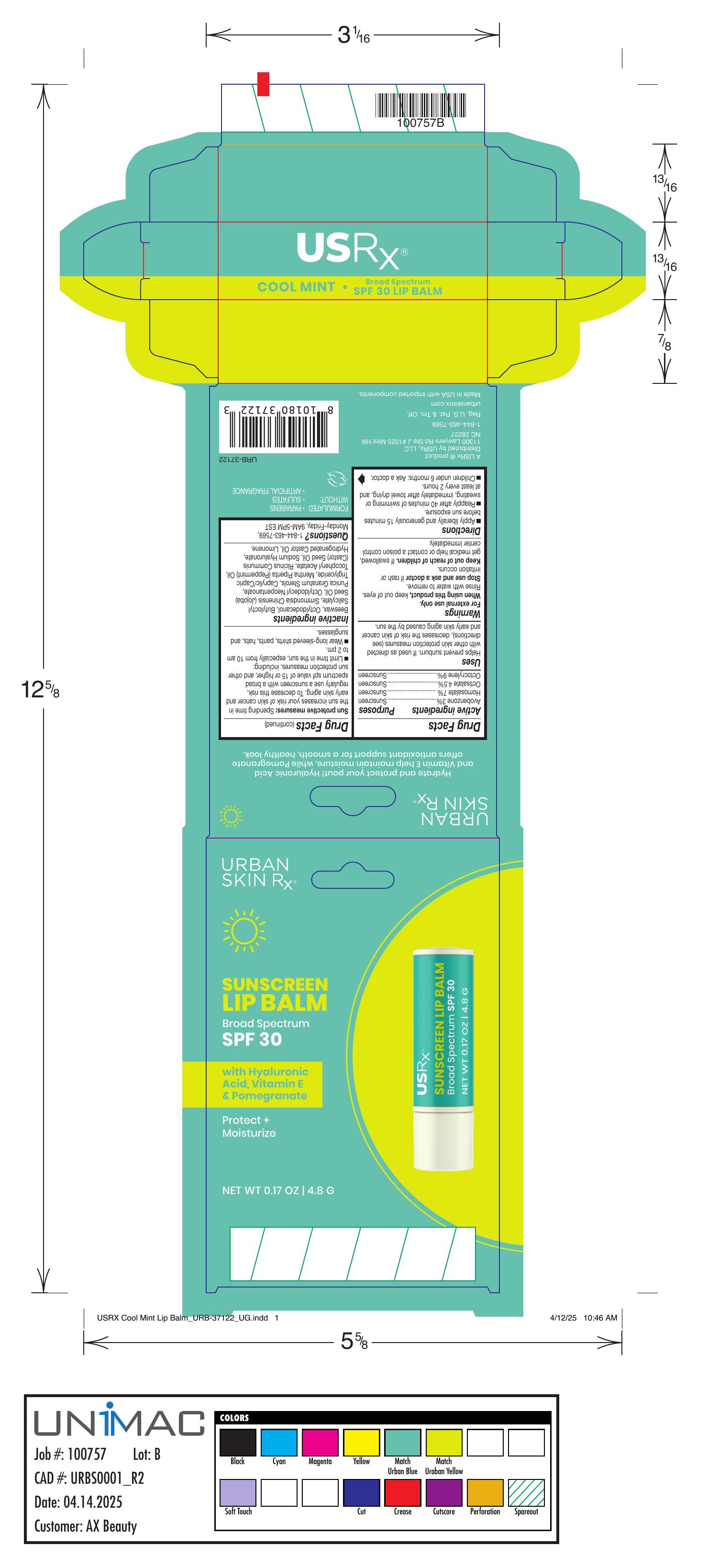 DRUG LABEL: Sunscreen Lip Balm SPF 30 Cool Mint
NDC: 70809-1235 | Form: STICK
Manufacturer: USRX
Category: otc | Type: HUMAN OTC DRUG LABEL
Date: 20250416

ACTIVE INGREDIENTS: AVOBENZONE 3 g/100 g; OCTOCRYLENE 9 g/100 g; OCTISALATE 4.5 g/100 g; HOMOSALATE 7 g/100 g
INACTIVE INGREDIENTS: OCTYLDODECYL NEOPENTANOATE; CAPRYLIC/CAPRIC TRIGLYCERIDE; BUTYLOCTYL SALICYLATE; .ALPHA.-TOCOPHEROL ACETATE; HYDROGENATED CASTOR OIL; BEESWAX; RICINUS COMMUNIS (CASTOR) SEED OIL; OCTYLDODECANOL; PUNICA GRANATUM STEROLS; LIMONENE, (+)-; SIMMONDSIA CHINENSIS (JOJOBA) SEED OIL; SODIUM HYALURONATE; PEPPERMINT OIL

Sunscreen Lip Balm SPF 30 Cool Mint

PURPOSE

Sunscreen

Keep out of reach of children. If swallowed get medical help or contact a poison control center immediately.

DOSAGE AND ADMINISTRATION

Directions • Apply liberally and generously 15 minutes before sun exposure. • Reapply after 40 minutes of swimming or sweating, immediately after towel drying, and at least every 2 hours. • Children under 6 months: Ask a doctor.
Sun protective measures: Spending time in the sun increases your risk of skin cancer and early skin aging. To decrease this risk, regularly use a sunscreen with a broad spectrum spf value of 15 or higher, and other sun protection measures, including: • Limit time in the sun, especially from 10 am to 2 pm. • Wear long-sleeve shirts, pants, hats, and sunglasses.

WARNINGS

For external use only

Stop use and ask a doctor if rash or irritation occurs

INACTIVE INGREDIENT

Beeswax, Octyldodecanol, Butyloctyl Salicylate, Simmondsia Chinensis (Jojoba) Seed Oil, Octyldodecyl Neopentanoate, Punica Granatum Sterols, Caprylic/Capric Triglyceride, Mentha Piperita (Peppermint) Oil, Tocopheryl Acetate, Hydrogenated Castor Oil, Ricinus Communis (Castor) Seed Oil, Sodium Hyaluronate, Flavor / Aroma, Limonene

When using this product keep out of eyes. Rinse with water